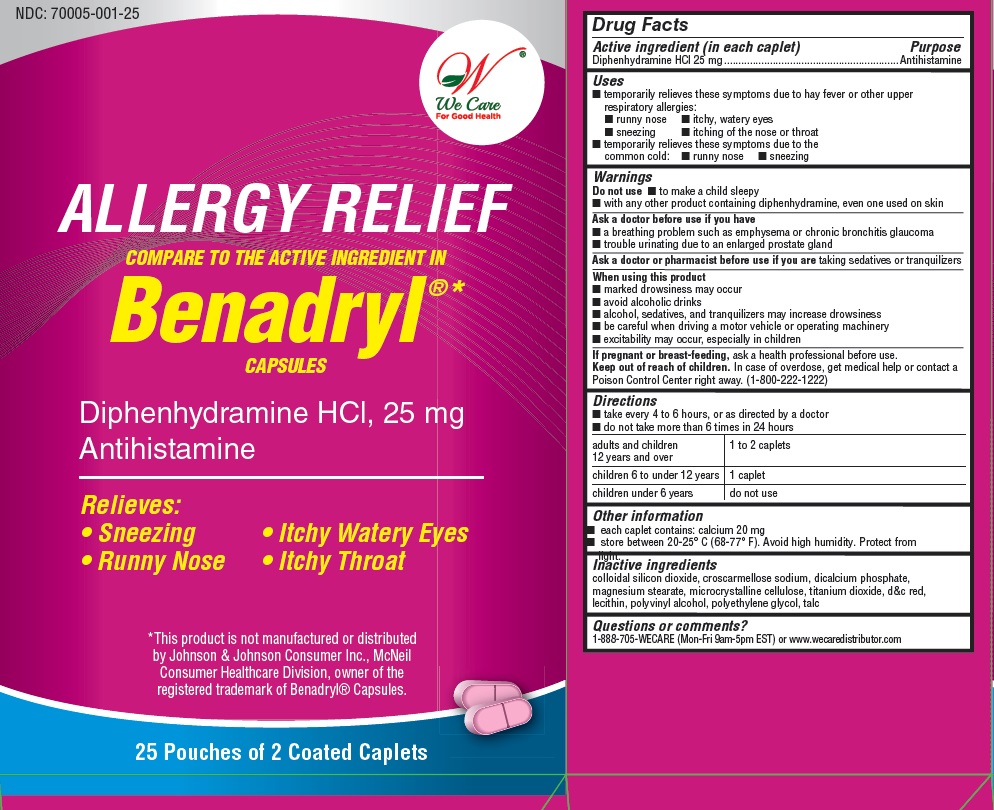 DRUG LABEL: Allergy Relief
                        
                        
                        
NDC: 70005-001 | Form: TABLET
Manufacturer: We Care Distributor Inc
Category: otc | Type: HUMAN OTC DRUG LABEL
Date: 20160202

ACTIVE INGREDIENTS: DIPHENHYDRAMINE HYDROCHLORIDE 25 mg/1 1
INACTIVE INGREDIENTS: SILICON DIOXIDE; CROSCARMELLOSE SODIUM; ANHYDROUS DIBASIC CALCIUM PHOSPHATE; MAGNESIUM STEARATE; CELLULOSE, MICROCRYSTALLINE; TITANIUM DIOXIDE; POLYVINYL ALCOHOL; POLYETHYLENE GLYCOLS; TALC; D&C RED NO. 27

Drug Facts

Active ingredient (in each caplet)

Diphenhydramine HCl 25 mg

Purpose

Antihistamine

Uses

- temporarily relieves these symptoms due to hay fever or other upper respiratory allergies:
  - runny nose
  - itchy, watery eyes
  - sneezing
  - itching of the nose or throat
- temporarily relieves these symptoms due to the common cold:
  - runny nose
  - sneezing

Warnings

Do not use

- to make a child sleepy
- with any other product containing diphenhydramine, even one used on skin

Ask a doctor before use if you have

- a breathing problem such as emphysema or chronic bronchitis glaucoma
- trouble urinating due to an enlarged prostate gland

Ask a doctor or pharmacist before use if you are

taking sedatives or tranquilizers

When using this product

- marked drowsiness may occur
- avoid alcoholic drinks
- alcohol, sedatives, and tranquilizers may increase drowsiness
- be careful when driving a motor vehicle or operating a machinery
- excitability may occur, especially in children

If pregnant or breast-feeding

ask a health professional before use.

Keep out of reach of children.

In case of overdose, get medical help or contact a Poison Control Center right away. (1-800-222-1222)

Directions

- take every 4 to 6 hours, or as directed by a doctor
- do not take more than 6 times in 24 hours
- adults and children 12 years and over - 1 to 2 caplets
- children 6 to under 12 years - 1 caplets
- children under 6 years - do not use

Other Information

- each caplet contains; calcium 20 mg
- store between 20-25 C (68-77 F), Avoid high humidity. Protect from light.

Inactive Ingredients

colloidal silicon dioxide, croscarmallose sodium, dicalcium phosphate, magnesium stearate, microcrystalline cellulose, titanium dioxide, d and c red, lecithin, polyvinyl alcohol, polyethylene glycol, talc.

Questions or comments?

Call: 1-800-705-WECARE (Mon-Fri 9am-5pm EST) or www.wecaredistributor.com

Principal Display Panel

NDC: 70005-001-25

We Care

For Good Health

ALLERGY RELIEF

COMPARE TO THE ACTIVE INGREDIENT IN

Benadryl

CAPSULES

TO OPEN PUSH IN TAB AND PULL OUT

Diphenhydramine HCL, 25 mg

Antihistamine

Relieves:

- Sneezing
- Itchy Watery Eyes
- Runny Nose
- Itchy Throat

This product is not manufactured or distributed by Johnson and Johnson Consumer Inc., McNeil Consumer Healthcare Division, owner of the registered trademark of Benadryl Capsules.

25 Pouches of 2 Coated Caplets